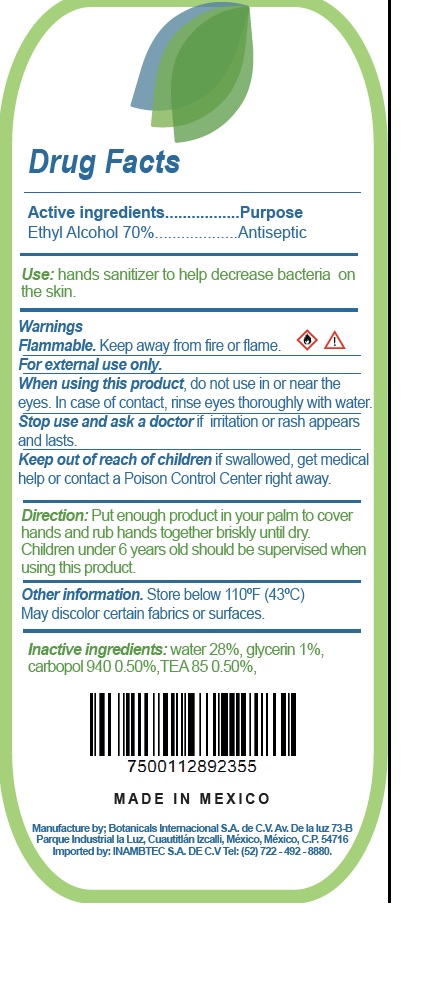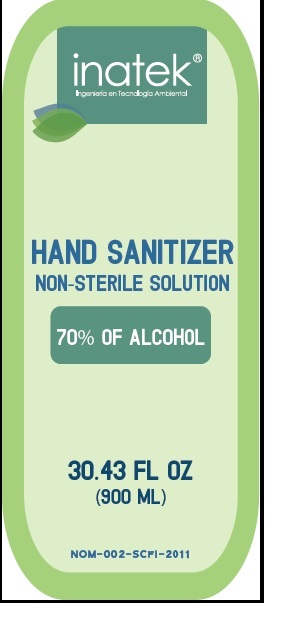 DRUG LABEL: HAND SANITIZER
NDC: 51384-002 | Form: GEL
Manufacturer: BOTANICALS INTERNACIONAL S.A. DE C.V
Category: otc | Type: HUMAN OTC DRUG LABEL
Date: 20200617

ACTIVE INGREDIENTS: ALCOHOL 70 mL/100 mL
INACTIVE INGREDIENTS: WATER 28 mL/100 mL; CARBOMER COPOLYMER TYPE A 0.5 mL/100 mL; GLYCERIN 1 mL/100 mL; TROLAMINE 0.5 mL/100 mL

INATEK 70% ALCOHOL BASED HAND SANITIZER

Active Ingredient

Ethyl Alcohol 70% v/v

Keep out of reach of children. If swallowed, get medical help or contact a Poison Control Center right away.

Purpose

Antiseptic

Warnings

- Flammable. Keep away from fire or flame.
- For external use only.

Directions

Direction:

- Put enough product in your palm to cover hands and rub hands together briskly until dry.
- Children under 6 years old should be supervised when using this product.

Uses

Use: hands sanitizer to help decrease bacteria on the skin

Stop use and ask a doctor if irritation or rash appears and lasts.

When using this product do not use in or near the eyes. In case of contact, rinse eyes thoroughly with water.

Inactive ingredients

water 28%, glycerin 1%, carbopol 940 0.50%,TEA 85 0.50%,

Other information

Store below 110oF (43oC)

May discolor certain fabrics

Principal Display Panel

NDC: 51384-002-01